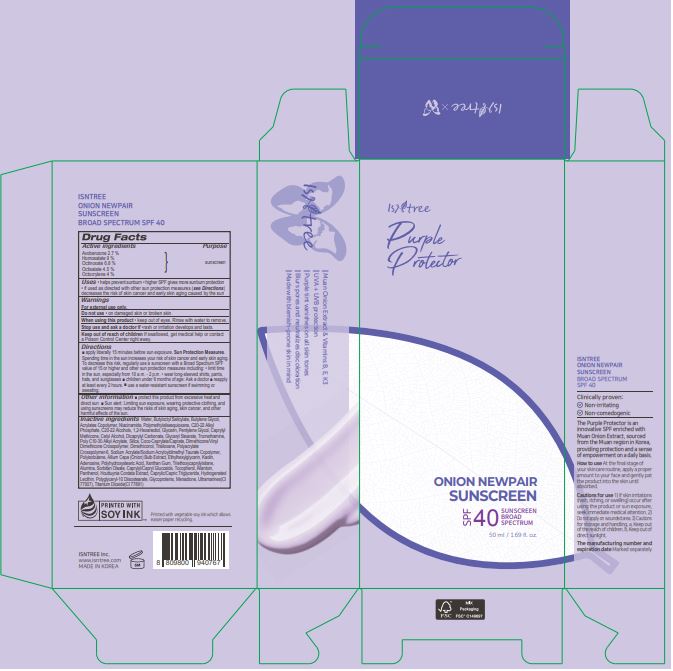 DRUG LABEL: ISNTREE ONION NEWPAIR SUNSCREEN
NDC: 81100-502 | Form: CREAM
Manufacturer: ISNTREE Inc.
Category: otc | Type: HUMAN OTC DRUG LABEL
Date: 20240723

ACTIVE INGREDIENTS: HOMOSALATE 4.5 g/50 mL; OCTINOXATE 3.4 g/50 mL; OCTISALATE 2.25 g/50 mL; OCTOCRYLENE 2 g/50 mL; AVOBENZONE 1.35 g/50 mL
INACTIVE INGREDIENTS: NIACINAMIDE; POLYMETHYLSILSESQUIOXANE (4.5 MICRONS); C20-22 ALCOHOLS; GLYCERIN; CETYL ALCOHOL; DICAPRYLYL CARBONATE; SILICON DIOXIDE; TITANIUM DIOXIDE; CAPRYLYL/CAPRYL OLIGOGLUCOSIDE; ALLANTOIN; PANTHENOL; HOUTTUYNIA CORDATA FLOWERING TOP; C20-22 ALKYL PHOSPHATE; WATER; XANTHAN GUM; TRIETHOXYCAPRYLYLSILANE; ALUMINUM OXIDE; TOCOPHEROL; TROMETHAMINE; PENTYLENE GLYCOL; CAPRYLYL TRISILOXANE; GLYCERYL MONOSTEARATE; TRISILOXANE; ONION; SORBITAN MONOOLEATE; ADENOSINE; COCOYL CAPRYLOCAPRATE; AMMONIUM ACRYLOYLDIMETHYLTAURATE, DIMETHYLACRYLAMIDE, LAURYL METHACRYLATE AND LAURETH-4 METHACRYLATE COPOLYMER, TRIMETHYLOLPROPANE TRIACRYLATE CROSSLINKED (45000 MPA.S); KAOLIN; MEDIUM-CHAIN TRIGLYCERIDES; ETHYLHEXYLGLYCERIN; BUTYLENE GLYCOL; MENADIONE; BUTYLOCTYL SALICYLATE; 1,2-HEXANEDIOL

ISNTREE ONION NEWPAIR SUNSCREEN

Active ingredients

Avobenzone 2.7 %
Homosalate 9 %
Octinoxate 6.8 %
Octisalate 4.5 %
Octocrylene 4 %

Purpose

sunscreen

Uses

• helps prevent sunburn • higher SPF gives more sunburn protection
• if used as directed with other sun protection measures (see Directions)
decreases the risk of skin cancer and early skin aging caused by the sun

Warnings

For external use only.

Do not use

• on damaged skin or broken skin.

When using this product

• keep out of eyes. Rinse with water to remove.

Stop use and ask a doctor if

•rash or irritation develops and lasts.

Keep out of reach of children

If swallowed, get medical help or contact
a Poison Control Center right away.

Directions

■ apply liberally 15 minutes before sun exposure. Sun Protection Measures.
Spending time in the sun increases your risk of skin cancer and early skin aging.
To decrease this risk, regularly use a sunscreen with a Broad Spectrum SPF
value of 15 or higher and other sun protection measures including: • limit time
in the sun, especially from 10 a.m. - 2 p.m. • wear long-sleeved shirts, pants,
hats, and sunglasses ■ children under 6 months of age: Ask a doctor ■ reapply
at least every 2 hours. ■ use a water-resistant sunscreen if swimming or
sweating.

Other information

■ protect the product from excessive heat and
direct sun ■ Sun alert: Limiting sun exposure, wearing protective clothing, and
using sunscreens may reduce the risks of skin aging, skin cancer, and other
harmful effects of the sun.

Inactive ingredients

Water, Butyloctyl Salicylate, Butylene Glycol, Acrylates Copolymer, Niacinamide, Polymethylsilsesquioxane, C20-22 Alkyl Phosphate, C20-22 Alcohols, 1,2-Hexanediol, Glycerin, Pentylene Glycol, Caprylyl Methicone, Cetyl Alcohol, Dicaprylyl Carbonate, Glyceryl Stearate, Tromethamine, Poly C10-30 Alkyl Acrylate, Silica, Coco-Caprylate/Caprate, Dimethicone/Vinyl Dimethicone Crosspolymer, Dimethiconol, Trisiloxane, Polyacrylate Crosspolymer-6, Sodium Acrylate/Sodium Acryloyldimethyl Taurate Copolymer, Polyisobutene, Allium Cepa (Onion) Bulb Extract, Ethylhexylglycerin, Kaolin, Adenosine, Polyhydroxystearic Acid, Xanthan Gum, Triethoxycaprylylsilane, Alumina, Sorbitan Oleate, Caprylyl/Capryl Glucoside, Tocopherol, Allantoin, Panthenol, Houttuynia Cordata Extract, Caprylic/Capric Triglyceride, Hydrogenated Lecithin, Polyglyceryl-10 Diisostearate, Glycoproteins, Menadione, Ultramarines(CI 77007), Titanium Dioxide(CI 77891)